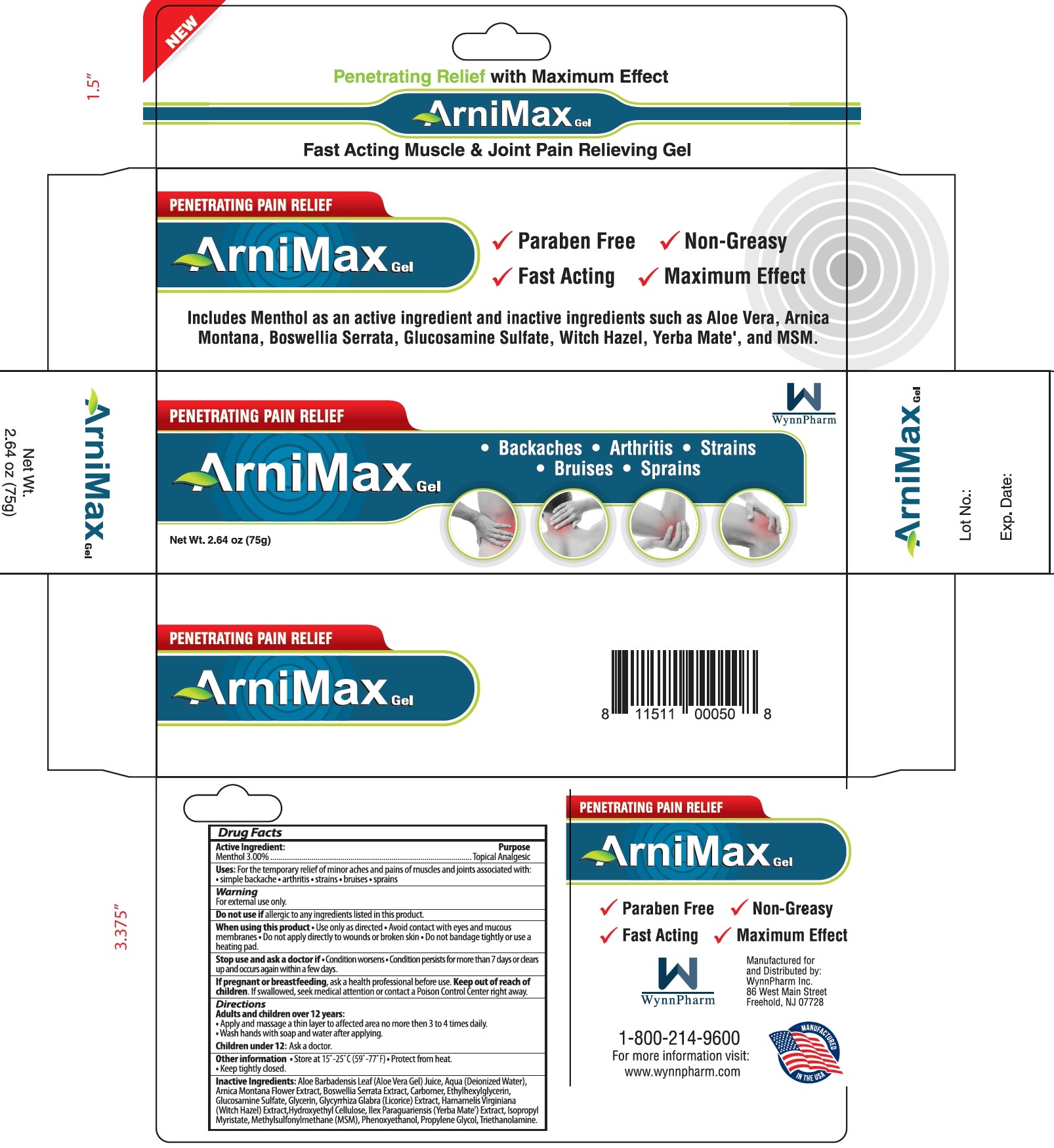 DRUG LABEL: ARNIMAX Penetrating Pain Relief Gel
NDC: 35324-274 | Form: GEL
Manufacturer: WYNNPHARM INC.
Category: otc | Type: HUMAN OTC DRUG LABEL
Date: 20231110

ACTIVE INGREDIENTS: MENTHOL 30 mg/1 g
INACTIVE INGREDIENTS: ALOE VERA LEAF; WATER; ARNICA MONTANA FLOWER; INDIAN FRANKINCENSE; CARBOMER HOMOPOLYMER, UNSPECIFIED TYPE; ETHYLHEXYLGLYCERIN; GLUCOSAMINE SULFATE; GLYCERIN; GLYCYRRHIZA GLABRA; HAMAMELIS VIRGINIANA TOP; HYDROXYETHYL CELLULOSE, UNSPECIFIED; ILEX PARAGUARIENSIS LEAF; ISOPROPYL MYRISTATE; DIMETHYL SULFONE; PHENOXYETHANOL; PROPYLENE GLYCOL; TROLAMINE

ARNIMAX Penetrating Pain Relief Gel

Active Ingredient:

Menthol 3.00%

Purpose

Topical Analgesic

Uses:

For the temporary relief of minor aches and pains of muscles and joints associated with: • simple backache • arthritis • strains • bruises • sprains

Warning

For external use only.

Do not use if

allergic to any ingredients listed in this product.

When using this product

• Use only as direcred • Avoid contact with eyes and mucous membranes • Do not apply directly to wounds or broken skin • Do not bandage tightly or use a heating pad.

Stop use and ask a doctor if

• Condition worsens • Condition persists for more than 7 days or clears up and occurs again within a few days.

If pregnant or breastfeeding,

ask a health professional before use.

Keep out of reach of children.

If swallowed, seek medical attention or contact a Poison Control Center right away.

Directions

Adults and children over 12 years:

• Apply and massage a thin layer to affected area no more than 3 to 4 times daily.

• Wash hands with soap and water after applying.

Ask a doctor. Children under 12:

Other information

• Store at 15°-25° C (59°-77°F) • Protect from heat. • Keep tightly closed.

Inactive Ingredients:

Aloe Barbadensis Leaf (Aloe Vera Gel) Juice, Aqua (Deionized Water), Arnica Montana Flower Extract, Boswellia Serrata Extract, Carbomer, Ethylhexylglycerin, Glucosamine Sulfate, Glycerin, GLycyrrhiza Glabra (Licorice) Extract, Hamamelis Virginiana (Witch Hazel) Extract, Hydroxyethyl Cellulose, Ilex Paraguariensis (Yerba Mate') Extract, Isopropyl Myristate, Methylsulfonulmethane (MSM), Phenoxyethanol, Propylene Glycol, Triethanolamine.